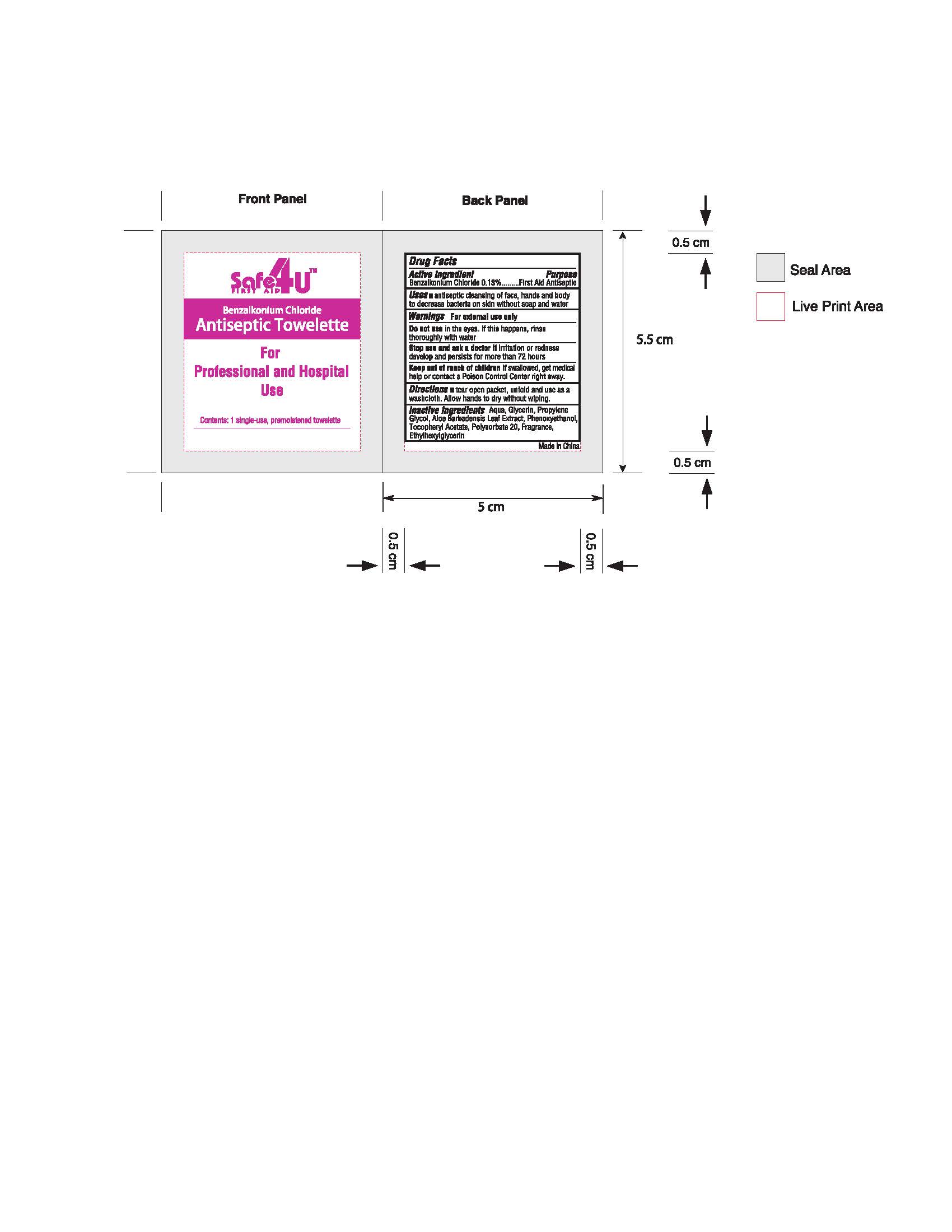 DRUG LABEL: antiseptic towelette
NDC: 82953-004 | Form: CLOTH
Manufacturer: Cosmuses Cosmetics (Ningbo) Co., Ltd.
Category: otc | Type: HUMAN OTC DRUG LABEL
Date: 20241204

ACTIVE INGREDIENTS: BENZALKONIUM CHLORIDE 0.13 g/100 1
INACTIVE INGREDIENTS: ALOE VERA LEAF; PHENOXYETHANOL; .ALPHA.-TOCOPHEROL ACETATE, DL-; WATER; GLYCERIN; POLYSORBATE 20; ETHYLHEXYLGLYCERIN; PROPYLENE GLYCOL

antiseptic towelette

Drug Fact

Active Ingredient

Benzalkonium Chloride 0.13%

Purpose

First Aid Antiseptic

Uses

antiseptic cleansig of face, hands and body to decrease bacteria on skin without soap and water.

Warning

For external use only.

Do not use in the eyes. If this happens, rinse thoroughly with water.

Stop use and ask a doctor if irritation or redness develop and persists for more than 72 hours.

Keep out of reach of children if swallowed, get medical help or contact a poison control center right away.

Directions

Tear open packet, unfold and use as a washcloth. Allow hand to dry without wiping.

Inactive Ingredients

Aqua, Glycerin, Propylene Glycol, Aloe Barbadensis Leaf Extract, Phenoxyethanol, Tocopheryl Acetate, Polysorbate 20, Fragrance, Ethylhexylglycerin